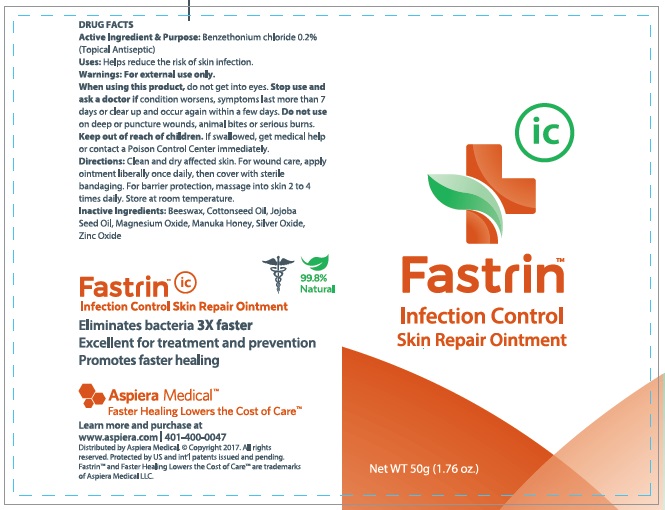 DRUG LABEL: Fastrin Infection Control Skin Repair
NDC: 24909-602 | Form: OINTMENT
Manufacturer: Aidance Skincare & Topical Solutions, LLC
Category: otc | Type: HUMAN OTC DRUG LABEL
Date: 20170601

ACTIVE INGREDIENTS: BENZETHONIUM CHLORIDE 0.2 g/100 g
INACTIVE INGREDIENTS: COTTONSEED OIL; HONEY; JOJOBA OIL; MAGNESIUM OXIDE; SILVER OXIDE; WHITE WAX; ZINC OXIDE

Drug Facts

Active Ingredient

Benzethonium Chloride 0.2%

Purpose

Topical Antiseptic

Uses

Helps reduce the risk of skin infection.

Warnings

For external use only. When using this product do not get into eyes. Stop use and ask a doctor if condition worsens, symptoms last more than 7 days or clear up and occur again within a few days. Do not use on deep or puncture wounds, animal bites or serious burns.

Keep out of reach of children.

If swallowed, get medical help or contact a Poison Control Center immediately.

Directions

Clean and dry affected skin. For wound care, apply ointment liberally at least once daily, then cover with sterile bandaging. For barrier protection, massage into skin 2 to 4 times daily. Store at room temperature.

Inactive Ingredients

Beeswax, Cottonseed Oil, Jojoba Seed Oil, Magnesium Oxide, Manuka Honey, Silver Oxide, Zinc Oxide

PRINCIPAL DISPLAY PANEL - 50g Tube

Fastrin

Infection Control

Skin Repair Ointment

Net WT 50g (1.76 oz.)